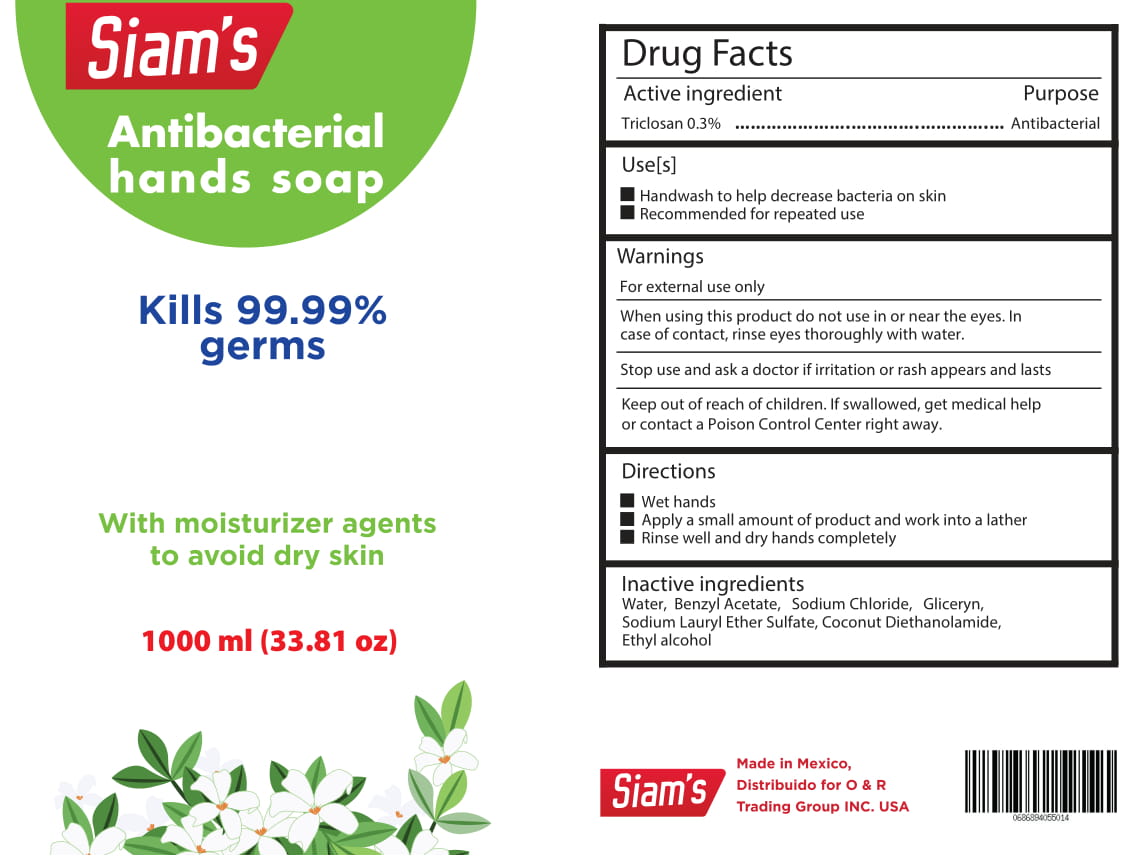 DRUG LABEL: SIAMS
NDC: 77830-112 | Form: LIQUID
Manufacturer: SUNI SUMINISTROS NACIONALES INTERNACIONALES Y DE SERVICIOS SA DE CV
Category: otc | Type: HUMAN OTC DRUG LABEL
Date: 20200606

ACTIVE INGREDIENTS: TRICLOSAN 3 g/1000 mL
INACTIVE INGREDIENTS: SODIUM CHLORIDE; COCO DIETHANOLAMIDE; ALCOHOL; GLYCERIN; BENZYL ACETATE; WATER; SODIUM LAURETH SULFATE

SIAMS HAND SOAP

Active Ingredient(s)

Triclosan 3% v/v

Purpose

Antibacterial

Use

Handwash to help reduce bacteria on the skin.

Recommended for repeated use.

Warnings

For external use only.

When using this product keep out of eyes, ears, and mouth. In case of contact with eyes, rinse eyes thoroughly with water.
Stop use and ask a doctor if irritation or rash occurs. These may be signs of a serious condition.
Keep out of reach of children. If swallowed, get medical help or contact a Poison Control Center right away.

Stop use and ask a doctor if irritation or rash occurs. These may be signs of a serious condition.

Keep out of reach of children. If swallowed, get medical help or contact a Poison Control Center right away.

Directions

Wet hands

Apply small amount of product and work into a lather

Rinse well and dry hand completely

Inactive ingredients

Water, Benzyl Acetate, Sodium Chloride, Glycerin, Sodium Lauryl Ether Sulfate, Coconut Diethanolamide, Ethyl Alcohol

Package Label - Principal Display Panel

1000 mL NDC:77830-112-12